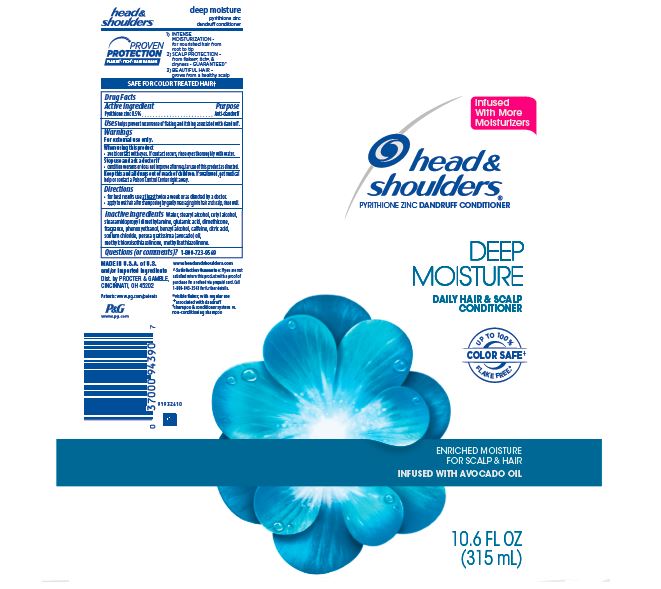 DRUG LABEL: Head and Shoulders Deep Moisture Hair and Scalp Conditioner
NDC: 69423-197 | Form: LOTION
Manufacturer: The Procter & Gamble Manufacturing Company
Category: otc | Type: HUMAN OTC DRUG LABEL
Date: 20251215

ACTIVE INGREDIENTS: PYRITHIONE ZINC 0.5 g/100 mL
INACTIVE INGREDIENTS: METHYLISOTHIAZOLINONE; CAFFEINE; AVOCADO OIL; WATER; STEARYL ALCOHOL; CETYL ALCOHOL; STEARAMIDOPROPYL DIMETHYLAMINE; GLUTAMIC ACID; DIMETHICONE; PHENOXYETHANOL; BENZYL ALCOHOL; CITRIC ACID MONOHYDRATE; SODIUM CHLORIDE; METHYLCHLOROISOTHIAZOLINONE

Head and Shoulders® Deep Moisture Hair and Scalp Conditioner
Classic Clean

Drug Facts

Active ingredient

Pyrithione zinc 0.5%

Purpose

Anti-dandruff

Uses

helps prevent recurrence of flaking and itching associated with dandruff.

Warnings

For external use only.

When using this product

- avoid contact with eyes. If contact occurs, rinse eyes thoroughly with water.

Stop use and ask a doctor if

- condition worsens or does not improve after regular use of this product as directed.

KEEP OUT OF REACH OF CHILDREN

Keep this and all drugs out of reach of children. If swallowed, get medical help or contact a Poison Control Center right away.

Directions

- for best results use at least twice a week or as directed by a doctor.
- apply to wet hair after shampooing by gently massaging into hair and scalp, rinse well.

Inactive ingredients

Water, stearyl alcohol, cetyl alcohol, stearamidopropyl dimethylamine, glutamic acid, dimethicone, fragrance, phenoxyethanol, benzyl alcohol, caffeine, citric acid, sodium chloride, persea gratissima (avocado) oil, methylchloroisothiazolinone, methylisothiazolinone.

Questions (or comments)?

1-800-723-9569

Dist. by PROCTER & GAMBLE,
CINCINNATI, OH 45202

PRINCIPAL DISPLAY PANEL - 315 mL Tube Label

head &
shoulders®

pyrithione zinc dandruff conditioner

deep moisture

DAILY HAIR & SCALP

CONDITIONER

enriched moisture for scalp & hair

infused with avocado oil

10.6 FL OZ (315 mL)